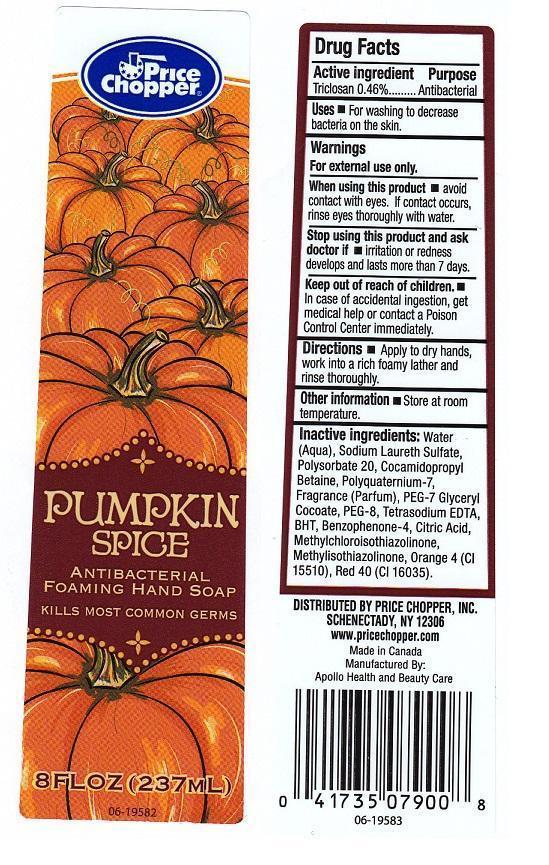 DRUG LABEL: PRICE CHOPPER
NDC: 63148-118 | Form: LIQUID
Manufacturer: APOLLO HEALTH AND BEAUTY CARE
Category: otc | Type: HUMAN OTC DRUG LABEL
Date: 20140606

ACTIVE INGREDIENTS: TRICLOSAN 4.6 mg/1 mL
INACTIVE INGREDIENTS: WATER; SODIUM LAURETH SULFATE; POLYSORBATE 20; COCAMIDOPROPYL BETAINE; POLYQUATERNIUM-7 (70/30 ACRYLAMIDE/DADMAC; 1600000 MW); PEG-7 GLYCERYL COCOATE; POLYETHYLENE GLYCOL 400; EDETATE SODIUM; BUTYLATED HYDROXYTOLUENE; SULISOBENZONE; METHYLCHLOROISOTHIAZOLINONE; METHYLISOTHIAZOLINONE; D&C ORANGE NO. 4; FD&C RED NO. 40; CITRIC ACID MONOHYDRATE

DRUG FACTS

ACTIVE INGREDIENT

TRICLOSAN 0.46%

PURPOSE

ANTIBACTERIAL

USES

FOR WASHING TO DECREASE BACTERIA ON THE SKIN

WARNINGS

FOR EXTERNAL USE ONLY

WHEN USING THIS PRODUCT

AVOID CONTACT WITH EYES. IF CONTACT OCCURS, RINSE EYES THOROUGHLY WITH WATER

STOP USING THIS PRODUCT AND ASK DOCTOR IF

IRRITATION OR REDNESS DEVELOPS AND LASTS MORE THAN 7 DAYS

KEEP OUT OF REACH OF CHILDREN

IN CASE OF ACCIDENTAL INGESTION, GET MEDICAL HELP OR CONTACT A POISON CONTROL CENTER IMMEDIATELY

DIRECTIONS

APPLY TO DRY HANDS, WORK INTO A RICH FOAMY LATHER AND RINSE THOROUGHLY

OTHER INFORMATION

STORE AT ROOM TEMPERATURE

INACTIVE INGREDIENTS

WATER (AQUA), SODIUM LAURETH SULFATE, POLYSORBATE 20, COCAMIDOPROPYL BETAINE, POLYQUATERNIUM-7, FRAGRANCE (PARFUM), PEG-7 GLYCERYL COCOATE, PEG-8, TETRASODIUM EDTA, BHT, BENZOPHENONE-4, CITRIC ACID, METHYLCHLOROISOTHIAZOLINONE, METHYLISOTHIAZOLINONE, ORANGE 4 (CI 15510), RED 40 (CI 16035)